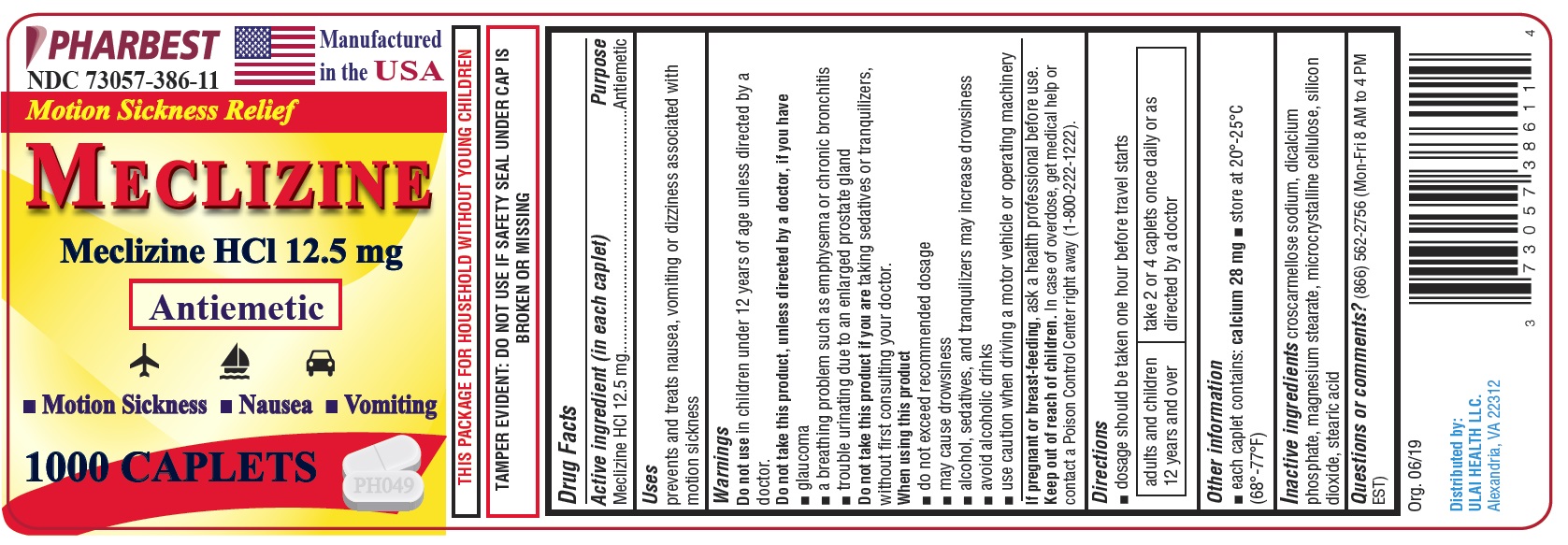 DRUG LABEL: MECLIZINE
NDC: 73057-386 | Form: TABLET
Manufacturer: Ulai Health LLC
Category: otc | Type: HUMAN OTC DRUG LABEL
Date: 20250120

ACTIVE INGREDIENTS: MECLIZINE HYDROCHLORIDE 12.5 mg/1 1
INACTIVE INGREDIENTS: CROSCARMELLOSE SODIUM; CALCIUM PHOSPHATE, DIBASIC, ANHYDROUS; MAGNESIUM STEARATE; CELLULOSE, MICROCRYSTALLINE; SILICON DIOXIDE; STEARIC ACID

Drug Facts

Active ingredient (in each caplet)

Meclizine HCl 12.5 mg

Purpose

Antiemetic

Uses

prevents and treats nausea, vomiting or dizziness associated with motion sickness

Do not use

in children under 12 years of age unless directed by a doctor.

Do not take this product, unless directed by a doctor, if you have

- glaucoma
- a breathing problem such as emphysema or chronic bronchitis
- trouble urinating due to an enlarged prostate gland

Do not take this product if you are taking sedatives or tranquilizers, without first consulting your doctor.

When using this product

- do not exceed recommended dosage
- may cause drowsiness
- alcohol, sedatives, and tranquilizers may increase drowsiness
- avoid alcoholic drinks
- use causion when driving a motor vehicle or operating machinery

If pregnant or breast-feeding,

ask a health professional before use.

Keep out of reach of children.

In case of overdose, get medical help or contact a Poison Control Center right away (1-800-222-1222).

Directions

- dosage should be taken one hour before travel starts

adults and children 12 years and over | take 2 or 4 caplets once daily or as directed by a doctor

Other information

- each caplet contains: calcium 28 mg
- store at 20o-25°C (68o-77°F)

Inactive ingredients

croscarmellose sodium, dicalcium phosphate, magnesium stearate, microcrystalline cellulose, silicon dioxide, stearic acid

Questions or comments?

(866) 562-2756 (Mon-Fri 8 AM to 4 PM EST)

PACKAGE LABEL

PHARBEST

NDC 73057-386-11

Manufactured in the USA

Motion Sickness Relief

MECLIZINE

Meclizine HCl 12.5 mg

Antiemetic

• Motion Sickness • Nausea • Vomiting

1000 CAPLETS